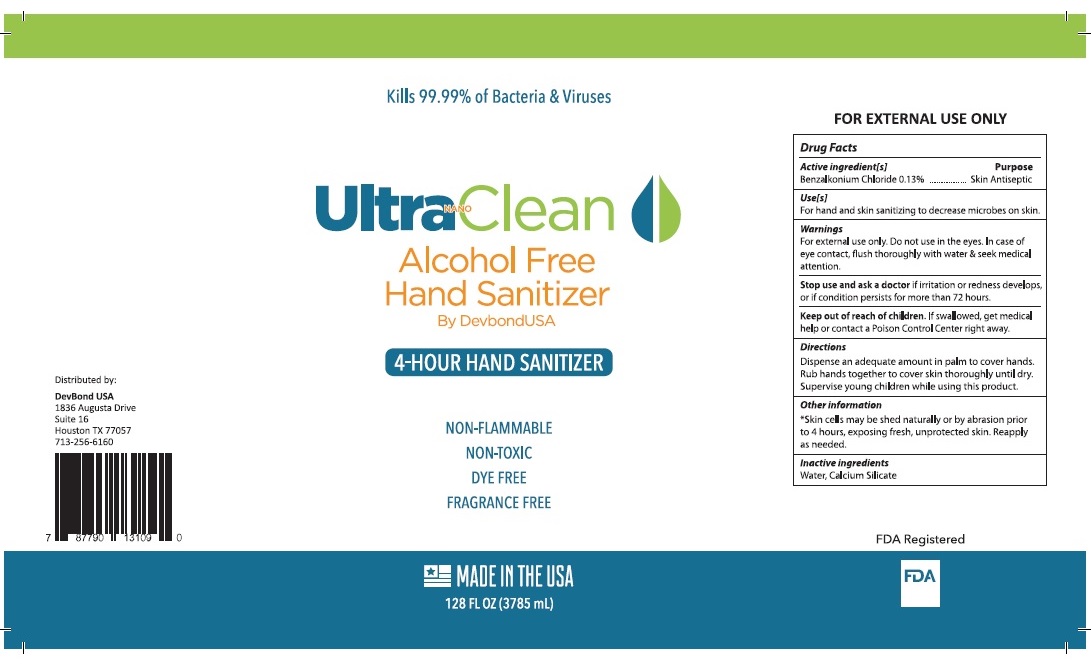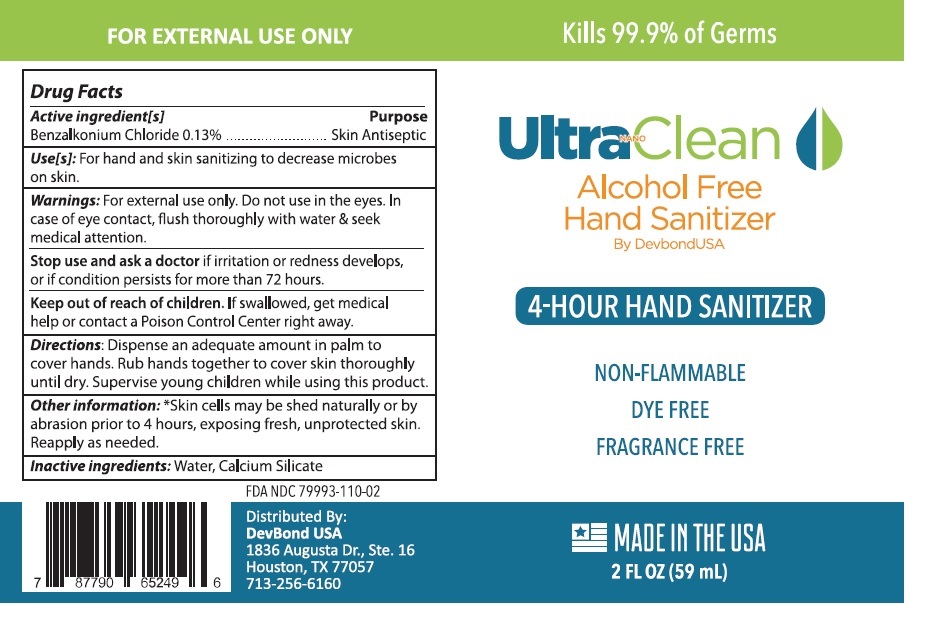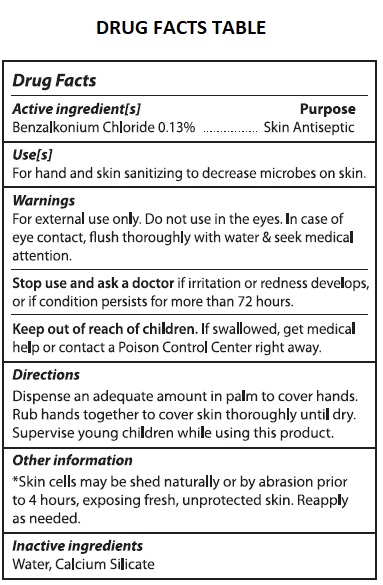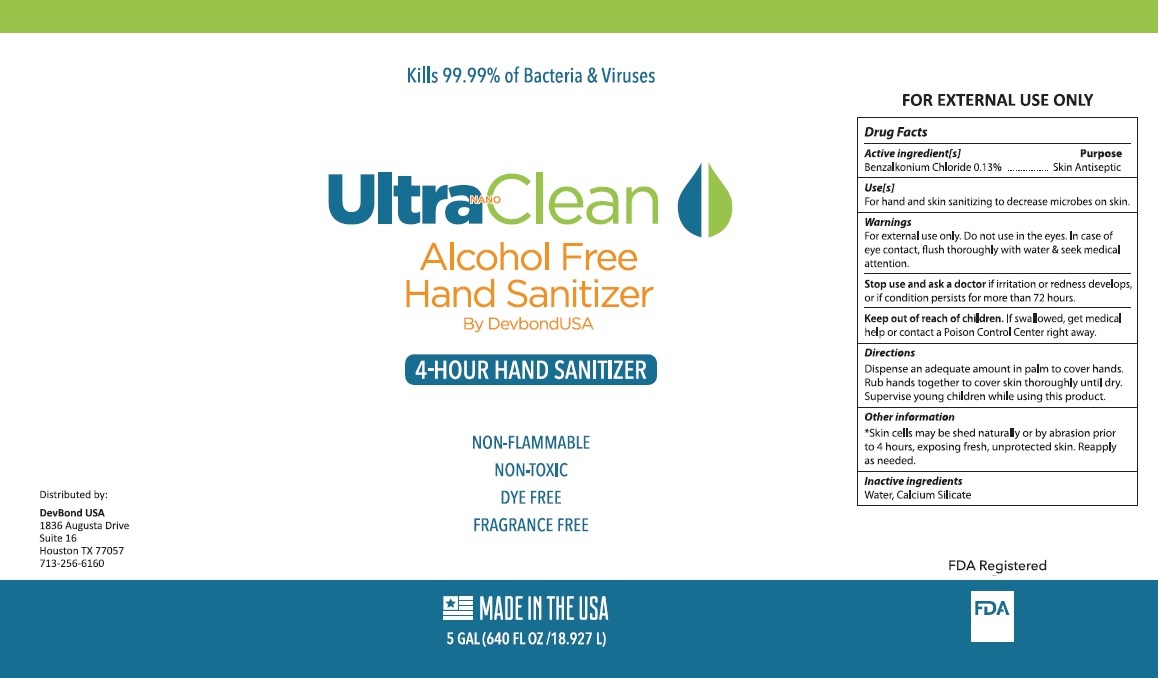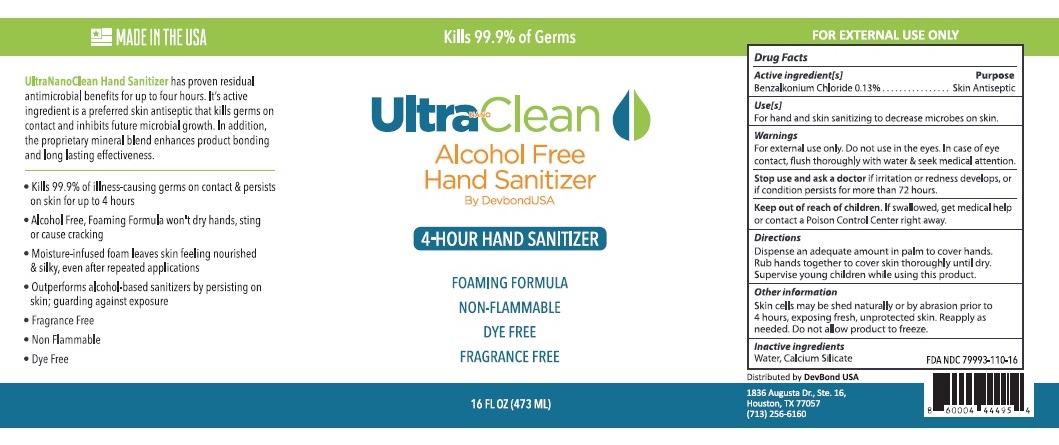 DRUG LABEL: Alcohol Free Hand Sanitizer
NDC: 79993-110 | Form: LIQUID
Manufacturer: Devbond Consulting, L.l.c
Category: otc | Type: HUMAN OTC DRUG LABEL
Date: 20210405

ACTIVE INGREDIENTS: BENZALKONIUM CHLORIDE 0.13 g/100 mL
INACTIVE INGREDIENTS: WATER; CALCIUM SILICATE

Ultra NANO Clean Alcohol Free Hand Sanitizer

Active ingredients[s]

Benzalkonium Chloride 0.13%

Purpose

Skin Antiseptic

Use[s]

For hand and skin sanitizing to decrease microbes on skin.

Warnings

For external use only. Do not use in the eyes. In case of eye contact, flush thoroughly with water & seek medical attention.

Stop use and ask a doctor if irritation or redness develops, or if condition persists for more than 72 hours.

Keep out of reach of children. If swallowed, get medical help or contact a Poison Control Center right away.

Directions

Dispense an adequate amount in palm to cover hands.

Rub hands together to cover skin thoroughly until dry.

Supervise young children while using this product.

Other information

*Skin cells may be shed naturally or by abrasion prior to 4 hours, exposing fresh, unprotected skin. Reapply as needed. Do not allow product to freeze.

Inactive ingredients

Water, Calcium Silicate

Kills 99.99% of Bacteria & Viruses

By DevbondUSA

4-HOUR HAND SANITIZER

NON-FLAMMABLE

NON-TOXIC

DYE FREE

FRAGRANCE FREE

UltraNanoClean Hand Sanitizer has proven residual antimicrobial benefits for up to four hours. It's active ingredient is a preferred skin antiseptic that kills germs on contacts and inhibits future microbial growth. In addition, the proprietary mineral blend enhances product bonding and long lasting effectiveness.

• Kills 99.9% of illness-causing germs on contact & persists on skin for up to 4 hours

• Alcohol Free, Foaming Formula won't dry hands, sting or cause cracking

• Moisture-infused foam leaves skin feeling nourished & silky, even after repeated applications

• Outperforms alcohol-based sanitizers by persisting on skin; guarding against exposure

MADE IN THE USA

Distributed by:

DevBond USA

1836 Augusta Drive

Suite 16

Houston TX 77057

(713) 256-6160

FOR EXTERNAL USE ONLY

FDA Registered